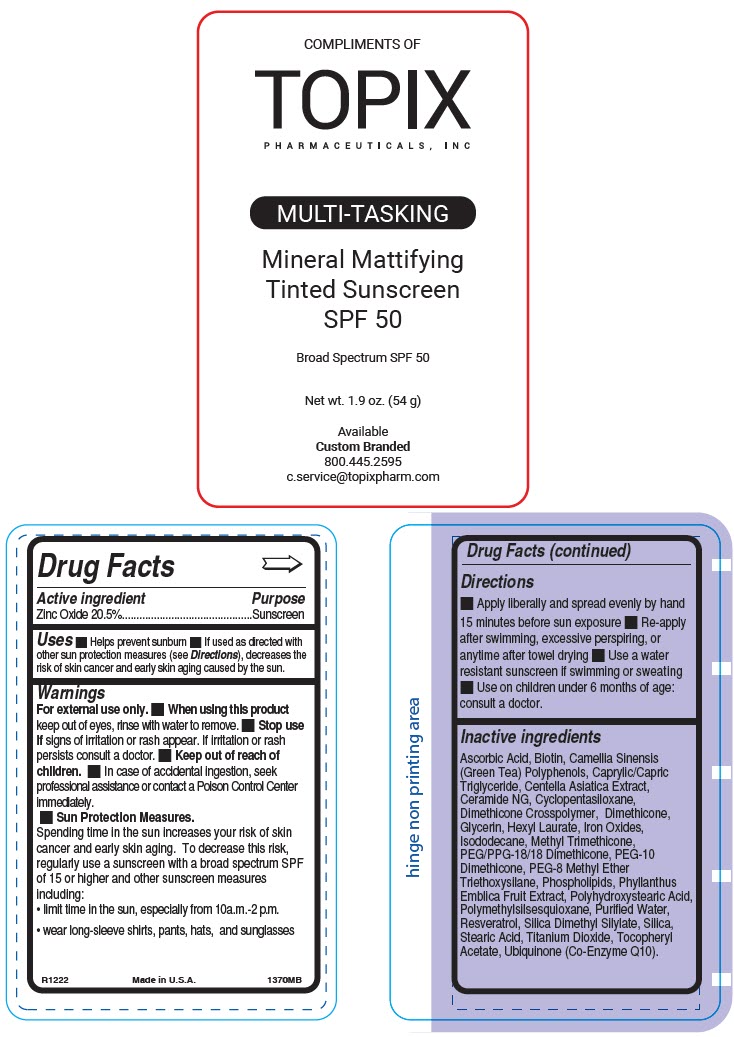 DRUG LABEL: Topix Mineral Mattifying Tinted Sunscreeninted 
NDC: 51326-370 | Form: LOTION
Manufacturer: Topiderm, Inc.
Category: otc | Type: HUMAN OTC DRUG LABEL
Date: 20230320

ACTIVE INGREDIENTS: ZINC OXIDE 205 mg/1 g
INACTIVE INGREDIENTS: ASCORBIC ACID; BIOTIN; GREEN TEA LEAF; MEDIUM-CHAIN TRIGLYCERIDES; CENTELLA ASIATICA WHOLE; CERAMIDE NG; CYCLOMETHICONE 5; DIMETHICONE CROSSPOLYMER (450000 MPA.S AT 12% IN CYCLOPENTASILOXANE); DIMETHICONE; GLYCERIN; HEXYL LAURATE; FERROUS OXIDE; ISODODECANE; METHYL TRIMETHICONE; PEG/PPG-18/18 DIMETHICONE; PEG-10 DIMETHICONE (600 CST); OMEGA-3 FATTY ACIDS; PHYLLANTHUS EMBLICA FRUIT; POLYHYDROXYSTEARIC ACID (2300 MW); POLYMETHYLSILSESQUIOXANE (4.5 MICRONS); WATER; RESVERATROL; SILICA DIMETHYL SILYLATE; SILICON DIOXIDE; STEARIC ACID; TITANIUM DIOXIDE; .ALPHA.-TOCOPHEROL ACETATE; UBIDECARENONE

Topix Mineral Mattifying Tinted Sunscreen
SPF 50

Drug Facts

Active ingredient

Zinc Oxide 20.5%

Purpose

Sunscreen

Uses

- Helps prevent sunburn
- If used as directed with other sun protection measures (see Directions), decreases the risk of skin cancer and early skin aging caused by the sun.

Warnings

For external use only.

- When using this product keep out of eyes, rinse with water to remove.

- Stop use if signs of irritation or rash appear. If irritation or rash persists consult a doctor.

- Keep out of reach of children.
- In case of accidental ingestion, seek professional assistance or contact a Poison Control Center immediately.

- Sun Protection Measures.
  Spending time in the sun increases your risk of skin cancer and early skin aging. To decrease this risk, regularly use a sunscreen with a broad spectrum SPF of 15 or higher and other sunscreen measures including:
  - limit time in the sun, especially from 10a.m.-2 p.m.
  - wear long-sleeve shirts, pants, hats, and sunglasses

Directions

- Apply liberally and spread evenly by hand 15 minutes before sun exposure
- Re-apply after swimming, excessive perspiring, or anytime after towel drying
- Use a water resistant sunscreen if swimming or sweating
- Use on children under 6 months of age: consult a doctor.

Inactive ingredients

Ascorbic Acid, Biotin, Camellia Sinensis (Green Tea) Polyphenols, Caprylic/Capric Triglyceride, Centella Asiatica Extract, Ceramide NG, Cyclopentasiloxane, Dimethicone Crosspolymer, Dimethicone, Glycerin, Hexyl Laurate, Iron Oxides, Isododecane, Methyl Trimethicone, PEG/PPG-18/18 Dimethicone, PEG-10 Dimethicone, PEG-8 Methyl Ether Triethoxysilane, Phospholipids, Phyllanthus Emblica Fruit Extract, Polyhydroxystearic Acid, Polymethylsilsesquioxane, Purified Water, Resveratrol, Silica Dimethyl Silylate, Silica, Stearic Acid, Titanium Dioxide, Tocopheryl Acetate, Ubiquinone (Co-Enzyme Q10).

PRINCIPAL DISPLAY PANEL - 54 g Bottle Label

COMPLIMENTS OF
TOPIX
PHARMACEUTICALS, INC

MULTI-TASKING

Mineral Mattifying
Tinted Sunscreen
SPF 50

Broad Spectrum SPF 50

Net wt. 1.9 oz. (54 g)

Available
Custom Branded
800.445.2595
c.service@topixpharm.com